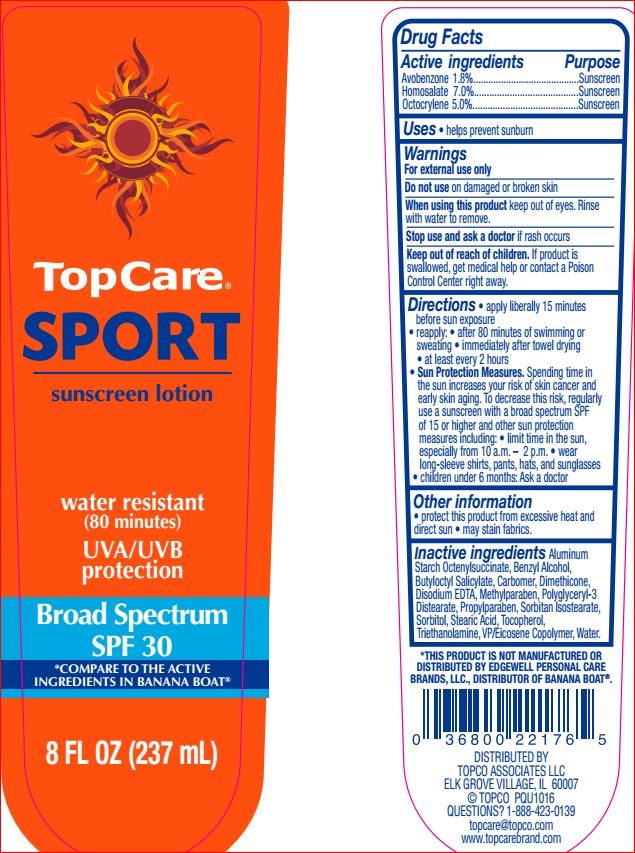 DRUG LABEL: Sport SPF 30
NDC: 36800-713 | Form: LOTION
Manufacturer: Top Care
Category: otc | Type: HUMAN OTC DRUG LABEL
Date: 20180703

ACTIVE INGREDIENTS: Avobenzone 1.8 g/100 mL; Homosalate 7 g/100 mL; Octocrylene 5 g/100 mL
INACTIVE INGREDIENTS: Aluminum Starch Octenylsuccinate; Benzyl Alcohol; Butyloctyl Salicylate; CARBOMER HOMOPOLYMER TYPE C (ALLYL PENTAERYTHRITOL CROSSLINKED); Dimethicone; EDETATE DISODIUM; Methylparaben; Polyglyceryl-3 Distearate; Propylparaben; Sorbitan Isostearate; Sorbitol; Stearic Acid; Tocopherol; TROLAMINE; EICOSYL POVIDONE; Water

Drug Facts

Active ingredients Purpose
Avobenzone 1.8%.............................Sunscreen
Homosalate 7.0%..............................Sunscreen
Octocrylene 5.0%.............................Sunscreen

INDICATIONS AND USAGE

Uses • helps prevent sunburn

Warnings
For external use only
Do not use on damaged or broken skin
When using this product keep out of eyes.
Rinse with water to remove.
Stop use and ask a doctor if rash occurs

Keep out of reach of children. If product is swallowed, get medical help or contact a Poison Control Center right away

DOSAGE AND ADMINISTRATION

Directions • apply liberally 15 minutes
before sun exposure • reapply: • after 80
minutes of swimming or sweating • immediately
after towel drying • at least every 2 hours
• Sun Protection Measures. Spending time in
the sun increases your risk of skin cancer and
early skin aging. To decrease this risk, regularly
use a sunscreen with a broad spectrum SPF
of 15 or higher and other sun protection
measures including: • limit time in the sun,
especially from 10 a.m. – 2 p.m. • wear
long-sleeve shirts, pants, hats, and sunglasses
• children under 6 months: Ask a doctor

Other information
• protect this product from excessive heat and direct sun • may stain fabrics.

Inactive ingredients

Water,
Butyloctyl Salicylate, Sorbitol, Aluminum
Starch Octenylsuccinate, VP/Eicosene
Copolymer, Stearic Acid, Benzyl Alcohol,
Carbomer, Dimethicone, Disodium EDTA,
Methylparaben, Polyglyceryl-3 Distearate,
Propylparaben, Sorbitan Isostearate,
Tocopherol, Triethanolamine.